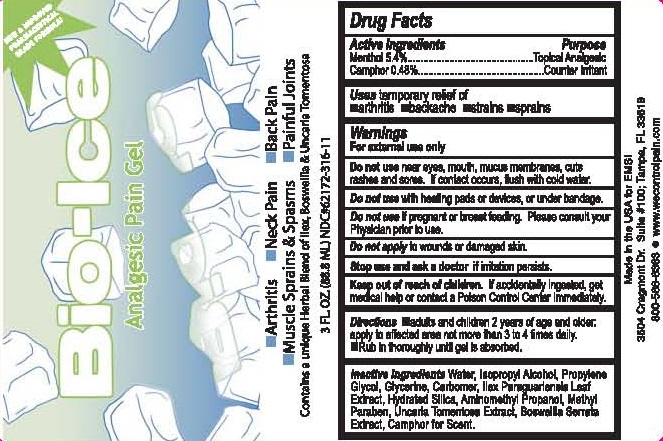 DRUG LABEL: BIO-ICE
NDC: 50130-316 | Form: GEL
Manufacturer: Electrostim Medical Services Inc. d/b/a EMSI
Category: otc | Type: HUMAN OTC DRUG LABEL
Date: 20251218

ACTIVE INGREDIENTS: MENTHOL 5.4 g/100 mL; CAMPHOR (SYNTHETIC) 0.48 g/100 mL
INACTIVE INGREDIENTS: WATER; ISOPROPYL ALCOHOL; PROPYLENE GLYCOL; GLYCERIN; CARBOMER HOMOPOLYMER TYPE C (ALLYL PENTAERYTHRITOL CROSSLINKED); ILEX PARAGUARIENSIS LEAF; HYDRATED SILICA; AMINOMETHYLPROPANOL; METHYLPARABEN; UNCARIA TOMENTOSA LEAF; BOSWELLIA SERRATA RESIN OIL; CAMPHOR OIL

BIO-ICE

ACTIVE INGREDIENTS

MENTHOL 5.4%

CAMPHOR 0.48%

PURPOSE

TOPICAL ANALGESIC

COUNTER IRRITANT

INDICATIONS AND USAGE

USES: TEMPORARY RELIEF OF

- ARTHRITIS
- BACKACHE
- STRAINS
- SPRAINS

WARNINGS

FOR EXTERNAL USE ONLY.

DO NOT USE NEAR EYES, MOUTH, MUCUS MEMBRANES, CUTS, RASHES AND SORES. IF CONTACT OCCURS, FLUSH WITH COLD WATER.

DO NOT USE WITH HEATING PADS OR DEVICES, OR UNDER BANDAGE.

DO NOT USE IF PREGNANT OR BREAST FEEDING. PLEASE CONSULT YOUR PHYSICIAN PRIOR TO USE.

DO NOT APPLY TO WOUNDS OR DAMAGED SKIN.

STOP USE AND ASK A DOCTOR IF IRRITATION PERSISTS.

KEEP OUT OF REACH OF CHILDREN. IF ACCIDENTALLY INGESTED, GET MEDICAL HELP OR CONTACT A POISON CONTROL CENTER IMMEDIATELY.

DIRECTIONS

- ADULTS AND CHILDREN 2 YEARS OF AGE AND OLDER: APPLY TO AFFECTED AREA NOT MORE THAN 3 TO 4 TIMES DAILY.
- RUB IN THOROUGHLY UNTIL GEL IS ABSORBED.

INACTIVE INGREDIENTS

WATER, ISOPROPYL ALCOHOL, PROPYLENE GLYCOL, GLYCERINE, CARBOMER, ILEX PARAGUARIENSIS LEAF EXTRACT, HYDRATED SILICA, AMINOMETHYL PROPANOL, METHYL PARABEN, UNCARIA TOMENTOSA EXTRACT, BOSWELLIA SERRATA EXTRACT, CAMPHOR FOR SCENT.